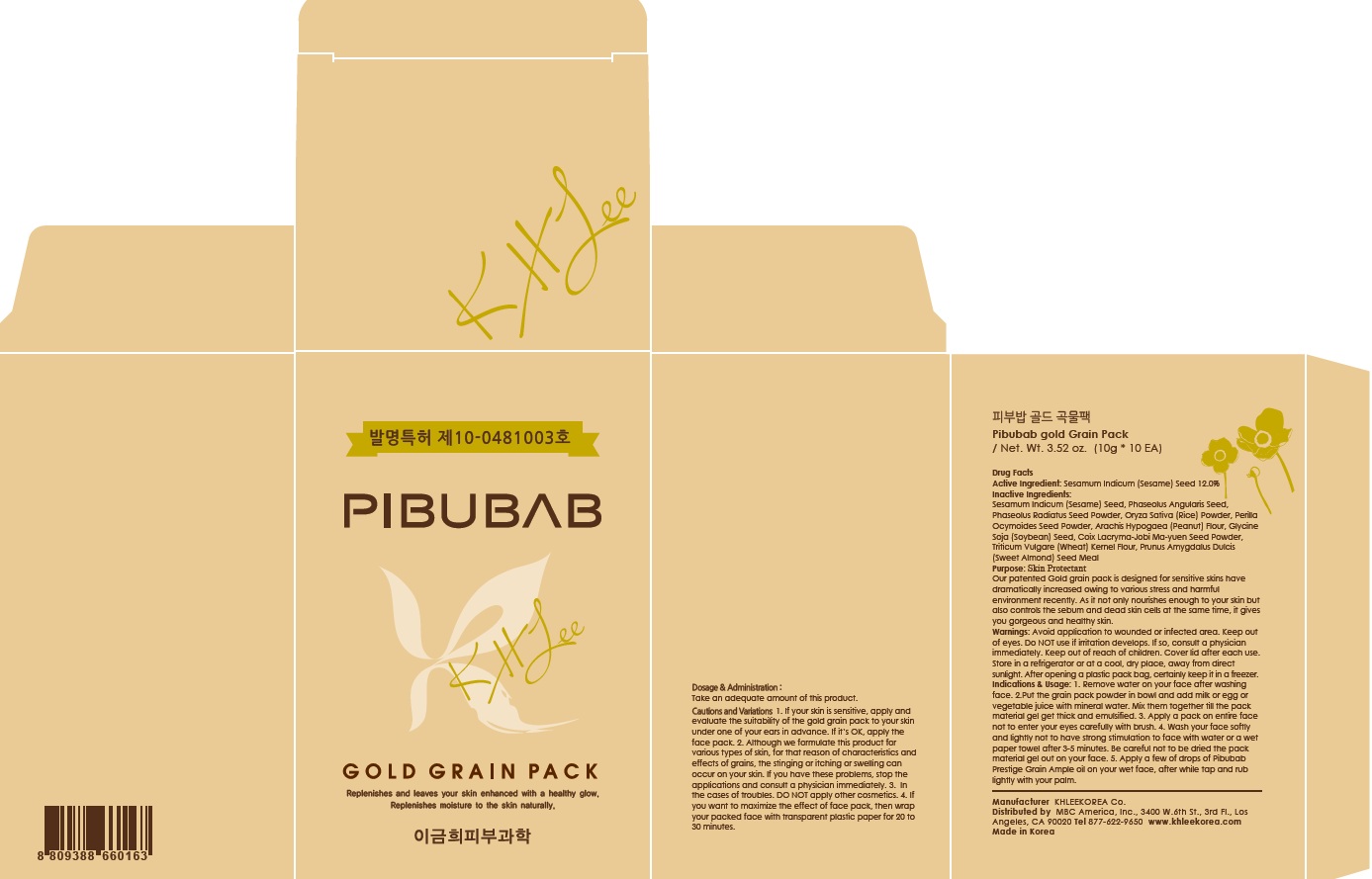 DRUG LABEL: Pibubab gold Grain Pack
NDC: 70567-020 | Form: POWDER
Manufacturer: KHLEEKOREA
Category: otc | Type: HUMAN OTC DRUG LABEL
Date: 20160418

ACTIVE INGREDIENTS: SESAME SEED 1.2 g/10 g
INACTIVE INGREDIENTS: ADZUKI BEAN; BEAN SPROUT

ACTIVE INGREDIENT

Active Ingredient: Sesamum Indicum (Sesame) Seed 12.0%

INACTIVE INGREDIENT

Inactive Ingredients: Phaseolus Angularis Seed, Phaseolus Radiatus Seed Powder, Oryza Sativa (Rice) Powder, Perilla Ocymoides Seed Powder, Arachis Hypogaea (Peanut) Flour, Glycine Soja (Soybean) Seed, Coix Lacryma-Jobi Ma-yuen Seed Powder, Triticum Vulgare (Wheat) Kernel Flour, Prunus Amygdalus Dulcis (Sweet Almond) Seed Meal

PURPOSE

Purpose: Skin Protectant

Our patented Gold grain pack is designed for sensitive skins have dramatically increased owing to various stress and harmful environment recently. As it not only nourishes enough to your skin but also controls the sebum and dead skin cells at the same time, it gives you gorgeous and healthy skin.

WARNINGS

Warnings: Avoid application to wounded or infected area. Keep out of eyes. Do NOT use if irritation develops. If so, consult a physician immediately. Keep out of reach of children. Cover lid after each use. Store in a refrigerator or at a cool, dry place, away from direct sunlight. After opening a plastic pack bag, certainly keep it in a freezer.

KEEP OUT OF REACH OF CHILDREN

INDICATIONS & USAGE

Indications & Usage: 1. Remove water on your face after washing face. 2. Put the grain pack powder in bowl and add milk or egg or vegetable juice with mineral water. Mix them together fill the pack material gel get thick and emulsified. 3. Apply a pack on entire face not to enter your eyes carefully with brush. 4. Wash your face softly and lightly not to have strong stimulation to face with water or a wet paper towel after 3~5 minutes. Be carefull not to be dried the pack materail gel out on your face. 5. Apply a few of drops of Pibubab Prestige Grain Ample oil on your wet face, after while tap and rub lightly with your palm.

DOSAGE & ADMINISTRATION

Dosage & Administration: Take an adequate amount of this product.